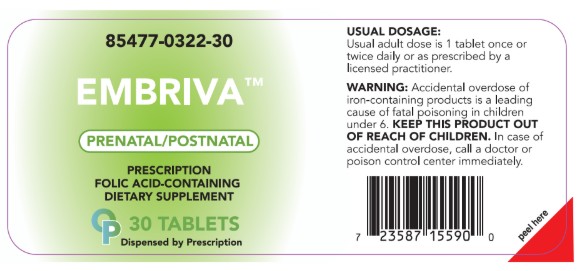 DRUG LABEL: Embriva
NDC: 85477-322 | Form: TABLET
Manufacturer: Oncora Pharma, LLC
Category: prescription | Type: HUMAN PRESCRIPTION DRUG LABEL
Date: 20250812

ACTIVE INGREDIENTS: PYRIDOXAL PHOSPHATE ANHYDROUS 2.5 mg/1 1; POTASSIUM IODIDE 0.15 mg/1 1; ASCORBIC ACID 125 mg/1 1; CHOLECALCIFEROL 0.0125 mg/1 1; THIAMINE 1.4 mg/1 1; FOLIC ACID 1 mg/1 1; METHYLCOBALAMIN 1 mg/1 1; CALCIUM CARBONATE 200 mg/1 1; FERROUS GLUCONATE 13 mg/1 1
INACTIVE INGREDIENTS: MAGNESIUM STEARATE; CELLULOSE, MICROCRYSTALLINE; SILICON DIOXIDE

Prenatal
Rx Only

DESCRIPTION

Each Tablet Contains:

Amount per Tablet

Thiamine (Vitamin B-1) (from Thiamine Mononitrate) ................. 1.4 mg

Ascorbic Acid...................... ......................................................... 125 mg

Folic Acid ....................................................................................... 1 mg

Colecalciferol ............................................................................. .0125 mg

Pyridoxal Phosphate Anhydrous ................................................. 2.5 mg

Methylcobalamin.................. ........................................................ 1 mg

Calcium Carbonate ................................................................... 200 mg

Ferrous Gluconate ..................................................................... 13 mg

Potassium Iodide........................................................................ .15 mg

Other ingredients: magnesium stearate, microcrystalline cellulose, silicone dioxide

INDICATIONS AND USAGE

Prenatal and Postnatal prescriptive Folic Acid

WARNINGS

WARNING: Accidental overdose of iron-containing products is a leading cause of fatal poisoning in children under age 6. Keep this product out of the reach of children. In case of accidental overdose, call a doctor or Poison Control Center immediately.

PRECAUTIONS

Call your licensed medical practitioner about side effects.

DOSAGE AND ADMINISTRATION

Usual adult dose is 1 tablet once or twice daily or as prescribed by a licensed practitioner.

HOW SUPPLIED

Bottles of 30: 85477-0322-30

Storage

KEEP THIS AND ALL MEDICATION OUR OF THE REACH OF CHILDREN.